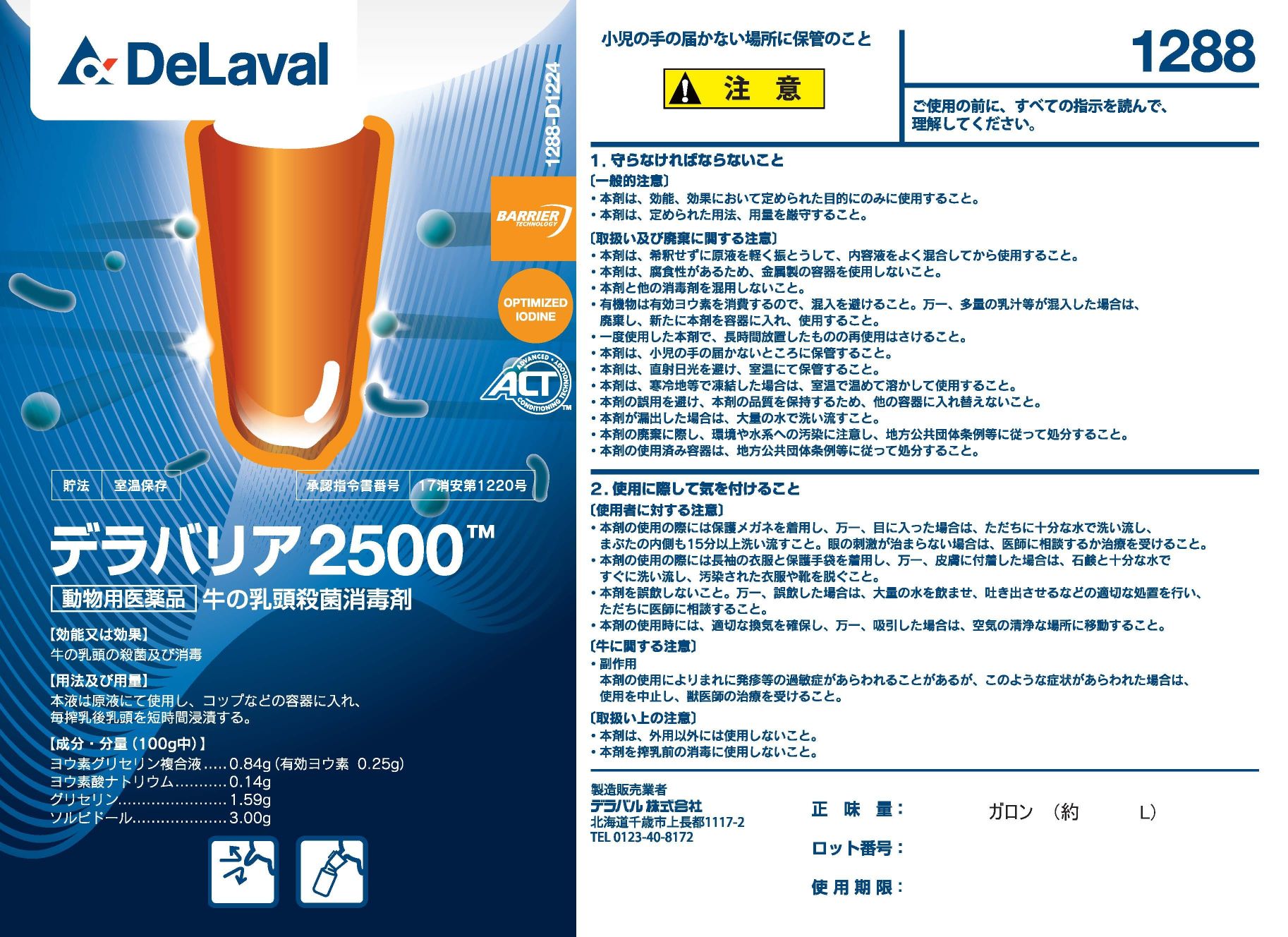 DRUG LABEL: Della Barrier 2500
NDC: 55756-783 | Form: SOLUTION
Manufacturer: DeLaval
Category: animal | Type: OTC ANIMAL DRUG LABEL
Date: 20260219

ACTIVE INGREDIENTS: Iodine 2.5 g/1 L
INACTIVE INGREDIENTS: GLYCERIN; SORBITOL SOLUTION 70%; SODIUM CHLORIDE; SODIUM IODATE; ANHYDROUS CITRIC ACID; SODIUM HYDROXIDE; poloxamer 335; POVIDONE K30; XANTHAN GUM

Della Barrier 2500

DELLA BARRIER 2500TM

Storage: Store at room temperature

Approval No.: 17 Shoan No. 1220

Veterinary medicinal product - Teat disinfectant for dairy cows

For disinfection and sanitization of bovine teats.

Use this product undiluted.

Pour the original solution into a cup or similar container and briefly immerse the teats after each milking.

Composition/Content (per 100 g)

Iodine-glycerin complex solution.........0.85 g (Available iodine 0.25 g)

Sodium iodate .................................0.14g

Glycerin...........................................1.59g

Sorbitol............................................3.00g

Precautions (to be strictly observed).

Use this product only for the purposes specified in the indications and effects. Follow the prescribed dosage and administration strictly. Shake the undiluted solution lightly before use to mix the contents thoroughly.
As the product is corrosive, do not use metal containers.Do not mix this product with other disinfectants.
Organic matter consumes available iodine; avoid contamination.
If a large amount of milk or other organic matter enters the container, discard the solution and refill with fresh product before use.
Do not reuse solution that has been left standing for a long time after use.
Keep Out of Reach of Children

Storage and Disposal

Store away from direct sunlight at room temperature.

If frozen in cold climates, warm the product to room temperature to thaw before use.

To avoid misuse and preserve product quality, do not transfer the contents to another container.

In case of leakage, wash away with plenty of water.

When disposing of the product, take care to avoid environmental and water-system contamination and follow local government regulations.

Precautions for Use

Wear protective goggles when using this product.

If it gets into the eyes, immediately rinse thoroughly with plenty of water - including under the eyelids - for at least 15 minutes.

If eye irritation persists, consult a physician or seek medical treatment.

Wear long-sleeved clothing and protective gloves.

If the product adheres to the skin, wash immediately with soap and plenty of water, and remove contaminated clothing and shoes.

Do not ingest this product.

If accidentally swallowed, administer plenty of water, induce vomiting as appropriate, and seek medical advice immediately.

Ensure adequate ventilation during use.

If vapors are inhaled, move the person to a place with fresh air.

Precautions for Cattle

Side effects: In rare cases, hypersensitivity reactions such as rash may occur.

If such symptoms appear, discontinue use and consult a veterinarian.

For external use only.

Do not use this product for pre-milking disinfection.

Net Volume:

Lot No:

Expiration Date:

Product Label image